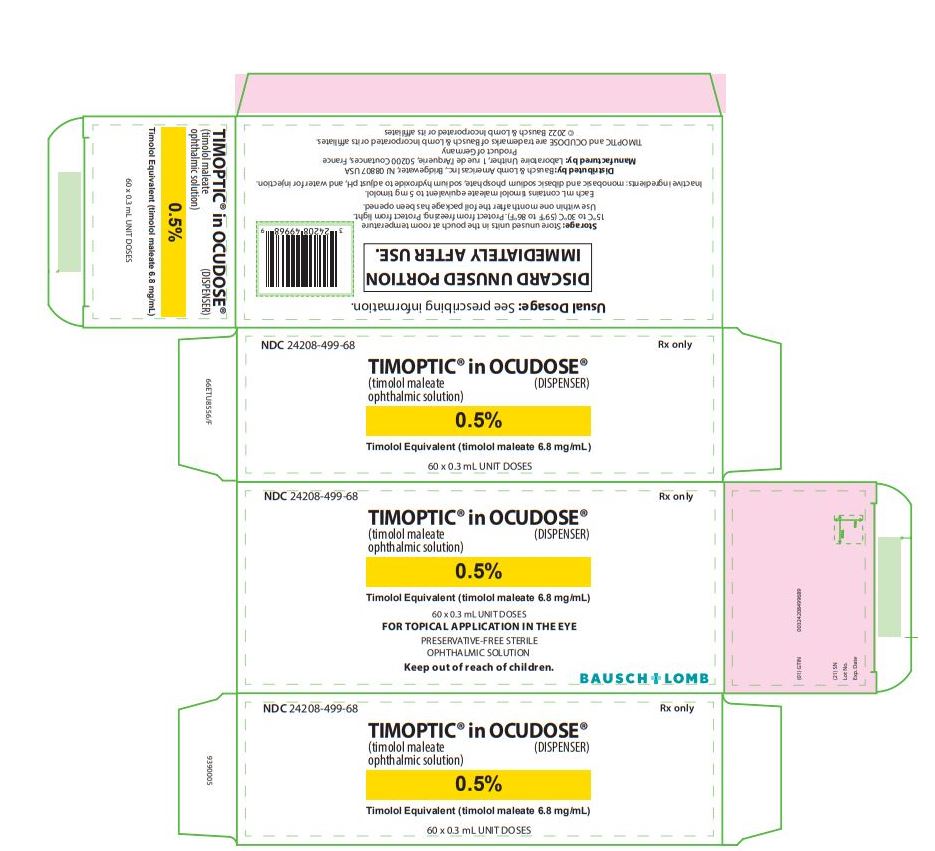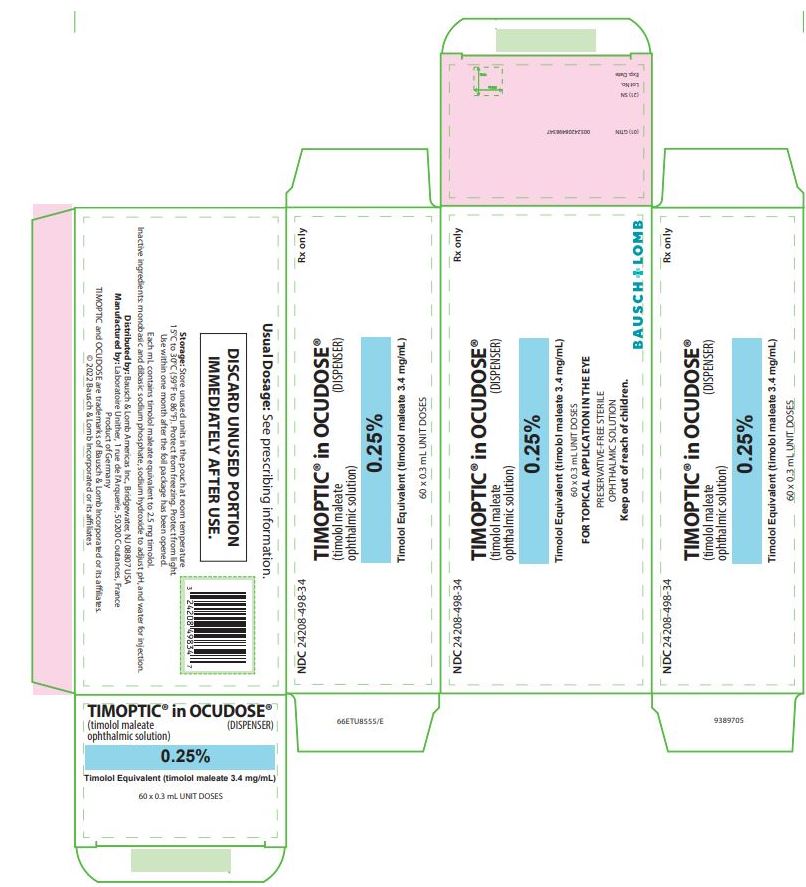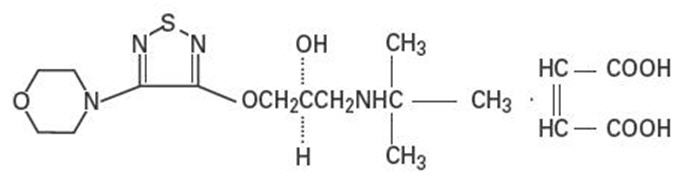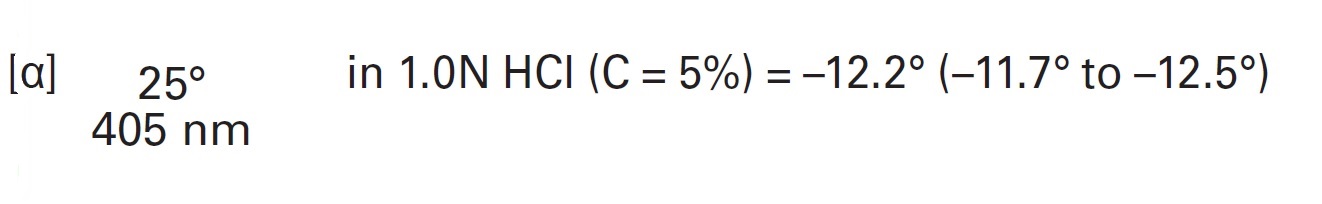 DRUG LABEL: Timoptic in Ocudose
NDC: 24208-498 | Form: SOLUTION
Manufacturer: Bausch & Lomb Incorporated
Category: prescription | Type: HUMAN PRESCRIPTION DRUG LABEL
Date: 20220131

ACTIVE INGREDIENTS: TIMOLOL MALEATE 3.4 mg/1 mL
INACTIVE INGREDIENTS: SODIUM PHOSPHATE, MONOBASIC, UNSPECIFIED FORM; SODIUM PHOSPHATE, DIBASIC, UNSPECIFIED FORM; Sodium Hydroxide; Water

TIMOPTIC® in OCUDOSE®
(timolol maleate ophthalmic solution)
0.25% and 0.5%

DESCRIPTION

Timolol maleate is a non-selective beta-adrenergic receptor blocking agent. Its chemical name is (-)-1-(tert-butylamino)-3-[(4-morpholino-1,2,5-thiadiazol-3-yl)oxy]-2-propanol maleate (1:1) (salt). Timolol maleate possesses an asymmetric carbon atom in its structure and is provided as the levo-isomer. The optical rotation of timolol maleate is:Its molecular formula is C13H24N4O3S•C4H4O4, and its structural formula is:

Timolol maleate has a molecular weight of 432.49. It is a white, odorless, crystalline powder which is soluble in water; sparingly soluble in ethanol; slightly soluble in chloroform; practically insoluble in ether. Timolol maleate is stable at room temperature.

Timolol maleate ophthalmic solution is supplied in two formulations: Ophthalmic Solution TIMOPTIC® (timolol maleate ophthalmic solution), which contains the preservative benzalkonium chloride; and Ophthalmic Solution TIMOPTIC (timolol maleate ophthalmic solution), the preservative-free formulation.

Preservative-free Ophthalmic Solution TIMOPTIC® is supplied in OCUDOSE®, a unit dose container, as a sterile, isotonic, buffered, aqueous solution of timolol maleate in two dosage strengths: Each mL of Preservative-free TIMOPTIC® in OCUDOSE® 0.25% contains 2.5 mg of timolol (3.4 mg of timolol maleate). The pH of the solution is approximately 7.0, and the osmolarity is 252-328 mOsm. Each mL of Preservative-free TIMOPTIC® in OCUDOSE® 0.5% contains 5 mg of timolol (6.8 mg of timolol maleate). Inactive ingredients: monobasic and dibasic sodium phosphate, sodium hydroxide to adjust pH, and water for injection.

CLINICAL PHARMACOLOGY

Mechanism of Action

Timolol maleate is a beta1 and beta2 (non-selective) adrenergic receptor blocking agent that does not have significant intrinsic sympathomimetic, direct myocardial depressant, or local anesthetic (membrane-stabilizing) activity.

Beta-adrenergic receptor blockade reduces cardiac output in both healthy subjects and patients with heart disease. In patients with severe impairment of myocardial function, beta-adrenergic receptor blockade may inhibit the stimulatory effect of the sympathetic nervous system necessary to maintain adequate cardiac function.

Beta-adrenergic receptor blockade in the bronchi and bronchioles results in increased airway resistance from unopposed parasympathetic activity. Such an effect in patients with asthma or other bronchospastic conditions is potentially dangerous.

TIMOPTIC (timolol maleate ophthalmic solution), when applied topically on the eye, has the action of reducing elevated as well as normal intraocular pressure, whether or not accompanied by glaucoma. Elevated intraocular pressure is a major risk factor in the pathogenesis of glaucomatous visual field loss. The higher the level of intraocular pressure, the greater the likelihood of glaucomatous visual field loss and optic nerve damage.

The onset of reduction in intraocular pressure following administration of TIMOPTIC (timolol maleate ophthalmic solution) can usually be detected within one-half hour after a single dose. The maximum effect usually occurs in one to two hours, and significant lowering of intraocular pressure can be maintained for periods as long as 24 hours with a single dose. Repeated observations over a period of one year indicate that the intraocular pressure-lowering effect of TIMOPTIC (timolol maleate ophthalmic
solution) is well maintained.

The precise mechanism of the ocular hypotensive action of TIMOPTIC (timolol maleate ophthalmic solution) is not clearly established at this time. Tonography and fluorophotometry studies in man suggest that its predominant action may be related to reduced aqueous formation. However, in some studies a slight increase in outflow facility was also observed.

Pharmacokinetics

In a study of plasma drug concentration in six subjects, the systemic exposure to timolol was determined following twice daily administration of TIMOPTIC 0.5%. The mean peak plasma concentration following morning dosing was 0.46 ng/mL and following afternoon dosing was 0.35 ng/mL.

Clinical Studies

In controlled multiclinic studies in patients with untreated intraocular pressures of 22 mmHg or greater, TIMOPTIC (timolol maleate ophthalmic solution) 0.25 or 0.5% administered twice a day produced a greater reduction in intraocular pressure than 1, 2, 3, or 4% pilocarpine solution administered four times a day or 0.5, 1, or 2% epinephrine hydrochloride solution administered twice a day.

In these studies, TIMOPTIC (timolol maleate ophthalmic solution) was generally well tolerated and produced fewer and less severe side effects than either pilocarpine or epinephrine. A slight reduction of resting heart rate in some patients receiving TIMOPTIC (timolol maleate ophthalmic solution) (mean reduction 2.9 beats/minute standard deviation 10.2) was observed.

INDICATIONS AND USAGE

Preservative-free TIMOPTIC in OCUDOSE is indicated in the treatment of elevated intraocular pressure in patients with ocular hypertension or open-angle glaucoma.

Preservative-free TIMOPTIC in OCUDOSE may be used when a patient is sensitive to the preservative in TIMOPTIC (timolol maleate ophthalmic solution), benzalkonium chloride, or when use of a preservative-free topical medication is advisable.

CONTRAINDICATIONS

Preservative-free TIMOPTIC in OCUDOSE is contraindicated in patients with (1) bronchial asthma; (2) a history of bronchial asthma; (3) severe chronic obstructive pulmonary disease (see WARNINGS); (4) sinus bradycardia; (5) second or third degree atrioventricular block; (6) overt cardiac failure (see WARNINGS); (7) cardiogenic shock; or (8) hypersensitivity to any component of this product.

WARNINGS

As with many topically applied ophthalmic drugs, this drug is absorbed systemically.

The same adverse reactions found with systemic administration of beta-adrenergic blocking agents may occur with topical administration. For example, severe respiratory reactions and cardiac reactions, including death due to bronchospasm in patients with asthma, and rarely death in association with cardiac failure, have been reported following systemic or ophthalmic administration of timolol maleate (see CONTRAINDICATIONS).

Cardiac Failure

Sympathetic stimulation may be essential for support of the circulation in individuals with diminished myocardial contractility, and its inhibition by beta-adrenergic receptor blockade may precipitate more severe failure.

In Patients without a History of Cardiac Failure continued depression of the myocardium with beta-blocking agents over a period of time can, in some cases, lead to cardiac failure. At the first sign or symptom of cardiac failure, Preservative-free TIMOPTIC in OCUDOSE should be discontinued.

Obstructive Pulmonary Disease
Patients with chronic obstructive pulmonary disease (e.g., chronic bronchitis, emphysema) of mild or moderate severity, bronchospastic disease, or a history of bronchospastic disease (other than bronchial asthma or a history of bronchial asthma, in which TIMOPTIC in OCUDOSE is contraindicated [see CONTRAINDICATIONS]) should, in general, not receive beta-blockers, including Preservative-free TIMOPTIC in OCUDOSE.

Major Surgery
The necessity or desirability of withdrawal of beta-adrenergic blocking agents prior to major surgery is controversial. Beta-adrenergic receptor blockade impairs the ability of the heart to respond to beta-adrenergically mediated reflex stimuli. This may augment the risk of general anesthesia in surgical procedures. Some patients receiving beta-adrenergic receptor blocking agents have experienced protracted severe hypotension during anesthesia. Difficulty in restarting and maintaining the heartbeat has also been reported. For these reasons, in patients undergoing elective surgery, some authorities recommend gradual withdrawal of beta-adrenergic receptor blocking agents.

If necessary during surgery, the effects of beta-adrenergic blocking agents may be reversed by sufficient doses of adrenergic agonists.

Diabetes Mellitus
Beta-adrenergic blocking agents should be administered with caution in patients subject to spontaneous hypoglycemia or to diabetic patients (especially those with labile diabetes) who are receiving insulin or oral hypoglycemic agents. Beta-adrenergic receptor blocking agents may mask the signs and symptoms of acute hypoglycemia.

Thyrotoxicosis
Beta-adrenergic blocking agents may mask certain clinical signs (e.g., tachycardia) of hyperthyroidism. Patients suspected of developing thyrotoxicosis should be managed carefully to avoid abrupt withdrawal of beta-adrenergic blocking agents that might precipitate a thyroid storm.

PRECAUTIONS

General

Because of potential effects of beta-adrenergic blocking agents on blood pressure and pulse, these agents should be used with caution in patients with cerebrovascular insufficiency. If signs or symptoms suggesting reduced cerebral blood flow develop following initiation of therapy with Preservative-free TIMOPTIC in OCUDOSE, alternative therapy should be considered.

Choroidal detachment after filtration procedures has been reported with the administration of aqueous suppressant therapy (e.g., timolol).

Angle-closure glaucoma:
In patients with angle-closure glaucoma, the immediate objective of treatment is to reopen the angle. This requires constricting the pupil. Timolol maleate has little or no effect on the pupil. TIMOPTIC in OCUDOSE should not be used alone in the treatment of angle-closure glaucoma.

Anaphylaxis:
While taking beta-blockers, patients with a history of atopy or a history of severe anaphylactic reactions to a variety of allergens may be more reactive to repeated accidental, diagnostic, or therapeutic challenge with such allergens. Such patients may be unresponsive to the usual doses of epinephrine used to treat anaphylactic reactions.

Muscle weakness:
Beta-adrenergic blockade has been reported to potentiate muscle weakness consistent with certain myasthenic symptoms (e.g., diplopia, ptosis, and generalized weakness). Timolol has been reported rarely to increase muscle weakness in some patients with myasthenia gravis or myasthenic symptoms.

Information for Patients

Patients should be instructed about the use of Preservative-free TIMOPTIC in OCUDOSE.

Since sterility cannot be maintained after the individual unit is opened, patients should be instructed to use the product immediately after opening and to discard the individual unit and any remaining contents immediately after use.

Patients with bronchial asthma, a history of bronchial asthma, severe chronic obstructive pulmonary disease, sinus bradycardia, second or third degree atrioventricular block, or cardiac failure should be advised not to take this product (see CONTRAINDICATIONS).

Drug Interactions

Although TIMOPTIC (timolol maleate ophthalmic solution) used alone has little or no effect on pupil size, mydriasis resulting from concomitant therapy with TIMOPTIC (timolol maleate ophthalmic solution) and epinephrine has been reported occasionally.

Beta-adrenergic blocking agents:
Patients who are receiving a beta-adrenergic blocking agent orally and Preservative-free TIMOPTIC in OCUDOSE should be observed for potential additive effects of beta-blockade, both systemic and on intraocular pressure. The concomitant use of two topical beta-adrenergic blocking agents is not recommended.

Calcium antagonists:
Caution should be used in the coadministration of beta-adrenergic blocking agents, such as Preservative-free TIMOPTIC in OCUDOSE, and oral or intravenous calcium antagonists, because of possible atrioventricular conduction disturbances, left ventricular failure, and hypotension. In patients with impaired cardiac function, coadministration should be avoided.

Catecholamine-depleting drugs:
Close observation of the patient is recommended when a beta-blocker is administered to patients receiving catecholamine-depleting drugs such as reserpine, because of possible additive effects and the production of hypotension and/or marked bradycardia, which may result in vertigo, syncope, or postural hypotension.

Digitalis and calcium antagonists:
The concomitant use of beta-adrenergic blocking agents with digitalis and calcium antagonists may have additive effects in prolonging atrioventricular conduction time.
CYP2D6 inhibitors:
Potentiated systemic beta-blockade (e.g., decreased heart rate, depression) has been reported during combined treatment with CYP2D6 inhibitors (e.g., quinidine, SSRIs) and timolol.

Clonidine:
Oral beta-adrenergic blocking agents may exacerbate the rebound hypertension which can follow the withdrawal of clonidine. There have been no reports of exacerbation of rebound hypertension with ophthalmic timolol maleate.

Injectable epinephrine:
(See PRECAUTIONS, General, Anaphylaxis)

Carcinogenesis, Mutagenesis, Impairment of Fertility

In a two-year study of timolol maleate administered orally to rats, there was a statistically significant increase in the incidence of adrenal pheochromocytomas in male rats administered 300 mg/kg/day (approximately 42,000 times the systemic exposure following the maximum recommended human ophthalmic dose). Similar differences were not observed in rats administered oral doses equivalent to approximately 14,000 times the maximum recommended human ophthalmic dose.

In a lifetime oral study in mice, there were statistically significant increases in the incidence of benign and malignant pulmonary tumors, benign uterine polyps and mammary adenocarcinomas in female mice at 500 mg/kg/day (approximately 71,000 times the systemic exposure following the maximum recommended human ophthalmic dose), but not at 5 or 50 mg/kg/day (approximately 700 or 7,000 times, respectively, the systemic exposure following the maximum recommended human ophthalmic dose). In a subsequent study in female mice, in which post-mortem examinations were limited to the uterus and the lungs, a statistically significant increase in the incidence of pulmonary tumors was again observed at 500 mg/kg/day.

The increased occurrence of mammary adenocarcinomas was associated with elevations in serum prolactin which occurred in female mice administered oral timolol at 500 mg/kg/day, but not at doses of 5 or 50 mg/kg/day. An increased incidence of mammary adenocarcinomas in rodents has been associated with administration of several other therapeutic agents that elevate serum prolactin, but no correlation between serum prolactin levels and mammary tumors has been established in humans. Furthermore, in adult human female subjects who received oral dosages of up to 60 mg of timolol maleate (the maximum recommended human oral dosage), there were no clinically meaningful changes in serum prolactin.

Timolol maleate was devoid of mutagenic potential when tested in vivo (mouse) in the micronucleus test and cytogenetic assay (doses up to 800 mg/kg) and in vitro in a neoplastic cell transformation assay (up to 100 mcg/mL). In Ames tests, the highest concentrations of timolol employed, 5,000 or 10,000 mcg/plate, were associated with statistically significant elevations of revertants observed with tester strain TA100 (in seven replicate assays), but not in the remaining three strains. In the assays with tester strain TA100, no consistent dose response relationship was observed, and the ratio of test to control revertants did not reach 2. A ratio of 2 is usually considered the criterion for a positive Ames test.

Reproduction and fertility studies in rats demonstrated no adverse effect on male or female fertility at doses up to 21,000 times the systemic exposure following the maximum recommended human ophthalmic dose.

Pregnancy:

Teratogenic effects

Teratogenicity studies with timolol in mice, rats and rabbits at oral doses up to 50 mg/kg/day (7,000 times the systemic exposure following the maximum recommended human ophthalmic dose) demonstrated no evidence of fetal malformations. Although delayed fetal ossification was observed at this dose in rats, there were no adverse effects on postnatal development of offspring. Doses of 1,000 mg/kg/day (142,000 times the systemic exposure following the maximum recommended human ophthalmic dose) were maternotoxic in mice and resulted in an increased number of fetal resorptions. Increased fetal resorptions were also seen in rabbits at doses of 14,000 times the systemic exposure following the maximum recommended human ophthalmic dose, in this case without apparent maternotoxicity.

There are no adequate and well-controlled studies in pregnant women. Preservative-free TIMOPTIC in OCUDOSE should be used during pregnancy only if the potential benefit justifies the potential risk to the fetus.

Nursing Mothers

Timolol maleate has been detected in human milk following oral and ophthalmic drug administration. Because of the potential for serious adverse reactions from timolol in nursing infants, a decision should be made whether to discontinue nursing or to discontinue the drug, taking into account the importance of the drug to the mother.

Pediatric Use

Safety and effectiveness of timolol maleate ophthalmic solution have been established when administered in pediatric patients aged 2 years and older. Use of timolol maleate ophthalmic solution in these children is supported by evidence from adequate and well-controlled studies in children and adults. Safety and efficacy in pediatric patients below the age of 2 years have not been established.

Geriatric Use

No overall differences in safety or effectiveness have been observed between elderly and younger patients.

ADVERSE REACTIONS

The most frequently reported adverse experiences have been burning and stinging upon instillation

(approximately one in eight patients).

The following additional adverse experiences have been reported less frequently with ocular administration of this or other timolol maleate formulations:

Body as a Whole

Headache, asthenia/fatigue, and chest pain.

Cardiovascular

Bradycardia, arrhythmia, hypotension, hypertension, syncope, heart block, cerebral vascular accident, cerebral ischemia, cardiac failure, worsening of angina pectoris, palpitation, cardiac arrest, pulmonary edema, edema, claudication, Raynaud's phenomenon, and cold hands and feet.

Digestive

Nausea, diarrhea, dyspepsia, anorexia, and dry mouth.

Immunologic

Systemic lupus erythematosus.

Nervous System/Psychiatric

Dizziness, increase in signs and symptoms of myasthenia gravis, paresthesia, somnolence, insomnia, nightmares, behavioral changes and psychic disturbances including depression, confusion, hallucinations, anxiety, disorientation, nervousness, and memory loss.

Skin

Alopecia and psoriasiform rash or exacerbation of psoriasis.

Hypersensitivity

Signs and symptoms of systemic allergic reactions including anaphylaxis, angioedema, urticaria, and localized and generalized rash.

Respiratory

Bronchospasm (predominantly in patients with pre-existing bronchospastic disease), respiratory failure, dyspnea, nasal congestion, cough and upper respiratory infections.

Endocrine

Masked symptoms of hypoglycemia in diabetic patients (see WARNINGS).

Special Senses

Signs and symptoms of ocular irritation including conjunctivitis, blepharitis, keratitis, ocular pain, discharge (e.g., crusting), foreign body sensation, itching and tearing, and dry eyes; ptosis; decreased corneal sensitivity; cystoid macular edema; visual disturbances including refractive changes and diplopia; pseudopemphigoid; choroidal detachment following filtration surgery (see PRECAUTIONS, General); and tinnitus.

Urogenital

Retroperitoneal fibrosis, decreased libido, impotence, and Peyronie’s disease.

The following additional adverse effects have been reported in clinical experience with ORAL timolol maleate or other ORAL beta-blocking agents, and may be considered potential effects of ophthalmic timolol maleate: Allergic: Erythematous rash, fever combined with aching and sore throat, laryngospasm with respiratory distress; Body as a Whole: Extremity pain, decreased exercise tolerance, weight loss; Cardiovascular: Worsening of arterial insufficiency, vasodilatation; Digestive: Gastrointestinal pain, hepatomegaly, vomiting, mesenteric arterial thrombosis, ischemic colitis; Hematologic: Nonthrombocytopenic purpura, thrombocytopenic purpura, agranulocytosis; Endocrine: Hyperglycemia, hypoglycemia; Skin: Pruritus, skin irritation, increased pigmentation, sweating; Musculoskeletal: Arthralgia; Nervous System/Psychiatric: Vertigo, local weakness, diminished concentration, reversible mental depression progressing to catatonia, an acute reversible syndrome characterized by disorientation for time and place, emotional lability, slightly clouded sensorium, and decreased performance on neuropsychometrics; Respiratory: Rales, bronchial obstruction; Urogenital: Urination difficulties.

To report SUSPECTED ADVERSE REACTIONS, contact Bausch & Lomb Incorporated at 1-800-553-5340 or FDA at 1-800-FDA-1088 or www.fda.gov/medwatch.

OVERDOSAGE

There have been reports of inadvertent overdosage with Ophthalmic Solution TIMOPTIC (timolol maleate ophthalmic solution) resulting in systemic effects similar to those seen with systemic beta-adrenergic blocking agents such as dizziness, headache, shortness of breath, bradycardia, bronchospasm, and cardiac arrest (see ADVERSE REACTIONS).

Overdosage has been reported with timolol maleate tablets. A 30-year-old female ingested 650 mg of timolol maleate tablets (maximum recommended oral daily dose is 60 mg) and experienced second and third degree heart block. She recovered without treatment but approximately two months later developed irregular heartbeat, hypertension, dizziness, tinnitus, faintness, increased pulse rate, and borderline first degree heart block.

An in vitro hemodialysis study, using ^14C timolol added to human plasma or whole blood, showed that timolol was readily dialyzed from these fluids; however, a study of patients with renal failure showed that timolol did not dialyze readily.

DOSAGE AND ADMINISTRATION

Preservative-free TIMOPTIC in OCUDOSE is a sterile solution that does not contain a preservative. The solution from one individual unit is to be used immediately after opening for administration to one or both eyes. Since sterility cannot be guaranteed after the individual unit is opened, the remaining contents should be discarded immediately after administration.

Preservative-free TIMOPTIC in OCUDOSE is available in concentrations of 0.25 and 0.5%. The usual starting dose is one drop of 0.25% Preservative-free TIMOPTIC in OCUDOSE in the affected eye(s) administered twice a day. Apply enough gentle pressure on the individual container to obtain a single drop of solution. If the clinical response is not adequate, the dosage may be changed to one drop of 0.5% solution in the affected eye(s) administered twice a day.

Since in some patients the pressure-lowering response to Preservative-free TIMOPTIC in OCUDOSE may require a few weeks to stabilize, evaluation should include a determination of intraocular pressure after approximately 4 weeks of treatment with Preservative-free TIMOPTIC in OCUDOSE.

If the intraocular pressure is maintained at satisfactory levels, the dosage schedule may be changed to one drop once a day in the affected eye(s). Because of diurnal variations in intraocular pressure, satisfactory response to the once-a-day dose is best determined by measuring the intraocular pressure at different times during the day.

Dosages above one drop of 0.5% TIMOPTIC (timolol maleate ophthalmic solution) twice a day generally have not been shown to produce further reduction in intraocular pressure. If the patient's intraocular pressure is still not at a satisfactory level on this regimen, concomitant therapy with other agent(s) for lowering intraocular pressure can be instituted taking into consideration that the preparation(s) used concomitantly may contain one or more preservatives. The concomitant use of two topical beta-adrenergic blocking agents is not recommended (see PRECAUTIONS, Drug Interactions, Beta-adrenergic blocking agents).

HOW SUPPLIED

Preservative-free Sterile Ophthalmic Solution TIMOPTIC® in OCUDOSE® is a clear, colorless to light yellow solution.

Preservative-free TIMOPTIC, 0.25% timolol equivalent, is supplied in OCUDOSE, a clear low density polyethylene unit dose container. Each individual unit contains 0.3 mL of solution, and is available in a foil laminate overwrapped pouch as follows:

NDC 24208-498-34; 60 Individual Unit Doses.

Preservative-free TIMOPTIC, 0.5% timolol equivalent, is supplied in OCUDOSE, a clear low density polyethylene unit dose container. Each individual unit contains 0.3 mL of solution, and is available in a foil laminate overwrapped pouch as follows:

NDC 24208-499-68; 60 Individual Unit Doses.

Storage

Store at room temperature, 15°C to 30°C (59°F to 86°F). Protect from freezing. Protect from light.

Because evaporation can occur through the unprotected polyethylene unit dose container and prolonged exposure to direct light can modify the product, the unit dose container should be kept in the protective foil overwrap and used within one month after the foil package has been opened.

Distributed by:
Bausch & Lomb Americas Inc.
Bridgewater, NJ 08807 USA

Manufactured by:
Laboratoire Unither

1 rue de l’Arquerie
50200 Coutances
France

TIMOPTIC and OCUDOSE are trademarks of Bausch & Lomb
Incorporated or its affiliates.

© 2022 Bausch & Lomb Incorporated or its affiliates

Revised: 01/2022
65NOT8556/D
9390305

PACKAGE/LABEL PRINCIPAL DISPLAY PANEL

NDC 24208-498-34
Rx only

TIMOPTIC® in OCUDOSE®

(timolol maleate ophthalmic solution)

(DISPENSER)

0.25%

Timolol Equivalent (Timolol Maleate 3.4 mg/mL)

60 x 0.3 mL UNIT DOSES

FOR TOPICAL APPLICATION IN THE EYE

PRESERVATIVE-FREE STERILE
OPHTHALMIC SOLUTION

Keep out of reach of children.

BAUSCH + LOMB

PACKAGE/LABEL PRINCIPAL DISPLAY PANEL

NDC 24208-499-68

Rx only

TIMOPTIC® in OCUDOSE®

(timolol maleate ophthalmic solution)

(DISPENSER)

0.5%

Timolol Equivalent (Timolol Maleate 6.8 mg/mL)

60 x 0.3 mL UNIT DOSES

FOR TOPICAL APPLICATION IN THE EYE

PRESERVATIVE-FREE STERILE

OPHTHALMIC SOLUTION

Keep out of reach of children.

BAUSCH + LOMB